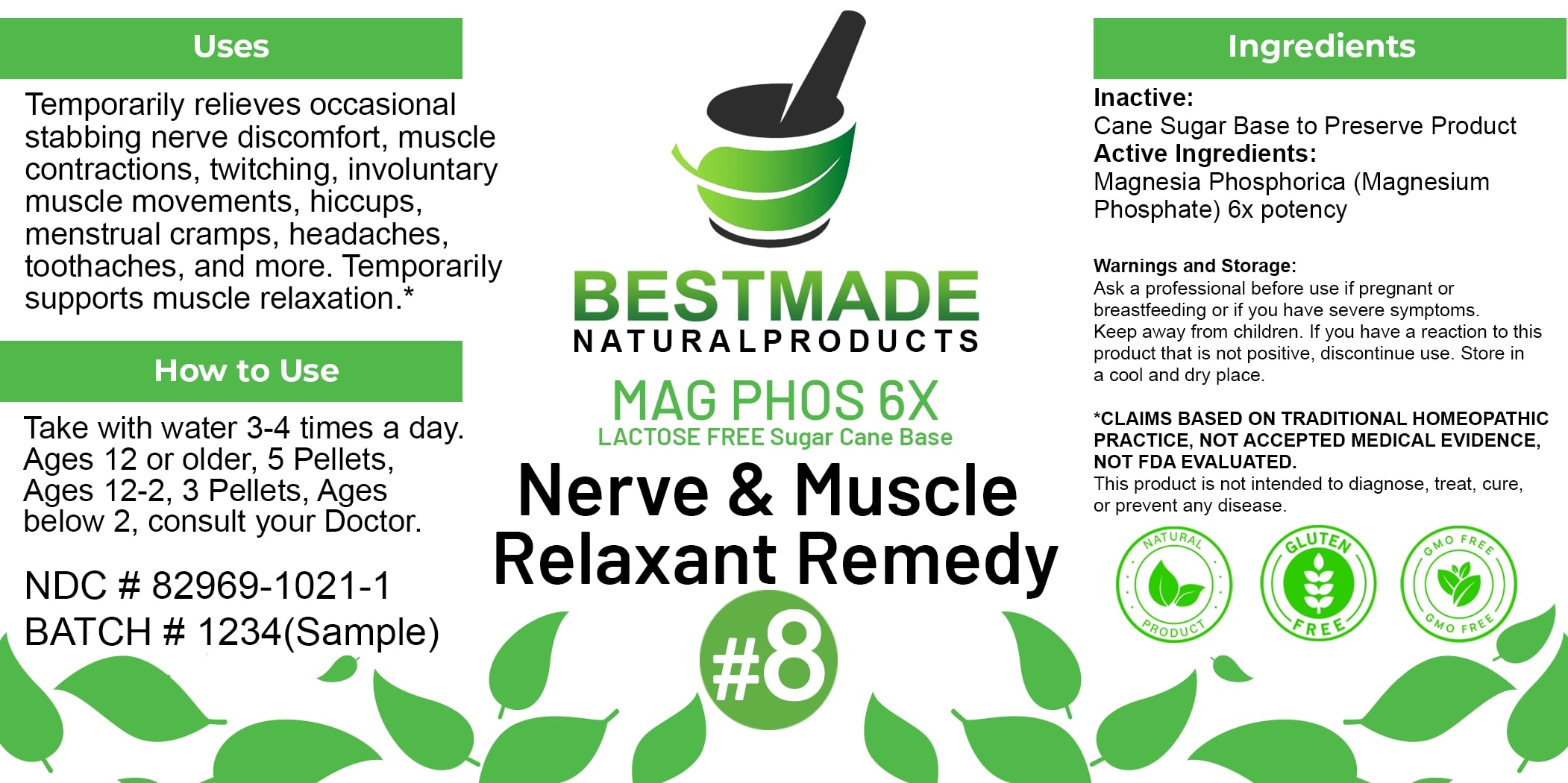 DRUG LABEL: Bestmade Natural Products Mag Phos (Lactose-Free)
NDC: 82969-1021 | Form: TABLET
Manufacturer: Bestmade Natural Products
Category: homeopathic | Type: HUMAN OTC DRUG LABEL
Date: 20250122

ACTIVE INGREDIENTS: MAGNESIUM PHOSPHATE, DIBASIC TRIHYDRATE 6 [hp_X]/6 [hp_X]
INACTIVE INGREDIENTS: SUCROSE 6 [hp_X]/6 [hp_X]

mag phos (lactose free)

DOSAGE AND ADMINISTRATION

How to Use

Take with water 3-4 times a day. Ages 12 or older, 5 Pellets, Ages 12-2, 3 Pellets, Ages below 2, consult your Doctor.

Uses

Temporarily relieves occasional stabbing nerve discomfort, muscle contractions, twitching, involuntary muscle movements, hiccups, menstrual cramps, headaches, toothaches, and more. Temporarily supports muscle relaxation.*

*CLAIMS BASED ON TRADITIONAL HOMEOPATHIC PRACTICE, NOT ACCEPTED MEDICAL EVIDENCE. NOT FDA EVALUATED. This product is not intended to diagnose, treat, cure, or prevent any disease.

Uses

Temporarily relieves occasional stabbing nerve discomfort, muscle contractions, twitching, involuntary muscle movements, hiccups, menstrual cramps, headaches, toothaches, and more. Temporarily supports muscle relaxation.*

*CLAIMS BASED ON TRADITIONAL HOMEOPATHIC PRACTICE, NOT ACCEPTED MEDICAL EVIDENCE. NOT FDA EVALUATED. This product is not intended to diagnose, treat, cure, or prevent any disease.

KEEP OUT OF REACH OF CHILDREN

Warnings and Storage:

Ask a professional before use if pregnant or breastfeeding or if you have severe symptoms. Keep away from children. If you have a reaction to this product that is not positive, discontinue use. Store in a cool and dry place.

Warnings and Storage:

Ask a professional before use if pregnant or breastfeeding or if you have severe symptoms. Keep away from children. If you have a reaction to this product that is not positive, discontinue use. Store in a cool and dry place.

*CLAIMS BASED ON TRADITIONAL HOMEOPATHIC PRACTICE, NOT ACCEPTED MEDICAL EVIDENCE. NOT FDA EVALUATED.

This product is not intended to diagnose, treat, cure, or prevent any disease.

INACTIVE INGREDIENT

Ingredients

Inactive: Cane Sugar Base to Preserve Product

ACTIVE INGREDIENT

Active Ingredients: Magnesia Phosphorica (Magnesium Phosphate) 6x potency

Entire package label